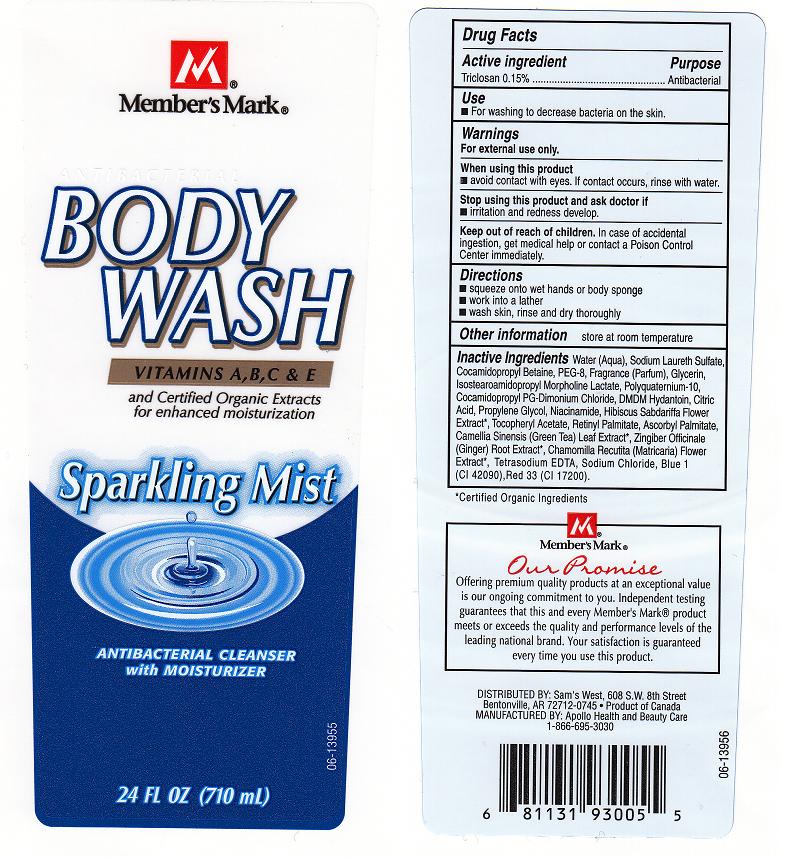 DRUG LABEL: SPARKLING MIST
NDC: 63148-804 | Form: LOTION
Manufacturer: Apollo Health and Beauty Care
Category: otc | Type: HUMAN OTC DRUG LABEL
Date: 20100715

ACTIVE INGREDIENTS: TRICLOSAN 0.15 mL/100 mL

DRUG FACTS BOX (BACK LABEL)

ACTIVE INGREDIENT

TRICLOSAN 0.15% (ANTIBACTERIAL)

USES AND DIRECTIONS

- USES: FOR WASHING TO DECREASE BACTERIA ON THE SKIN.
- DIRECTIONS: SQUEEZE ONTO WET HANDS OR BODY SPONGE, WORK INTO A LATHER, WASH SKIN, RINSE AND DRY THOROUGHLY

WARNINGS

- FOR EXTERNAL USE ONLY

WHEN USING THIS PRODUCT

- AVOID CONTACT WITH EYES. IF CONTACT OCCURS, RINSE WITH WATER.

STOP USING THIS PRODUCT AND ASK DOCTOR IF

- IRRITATION AND REDNESS DEVELOPS.

KEEP OUT OF REACH OF CHILDREN

- IN CASE OF ACCIDENTAL INGESTION, GET MEDICAL HELP OR CONTACT A POISON CONTROL CENTER IMMEDIATELY.

PACKAGE FRONT AND BACK LABELS

24OZ FRONT AND BACK LABELS: mmark24.jpg